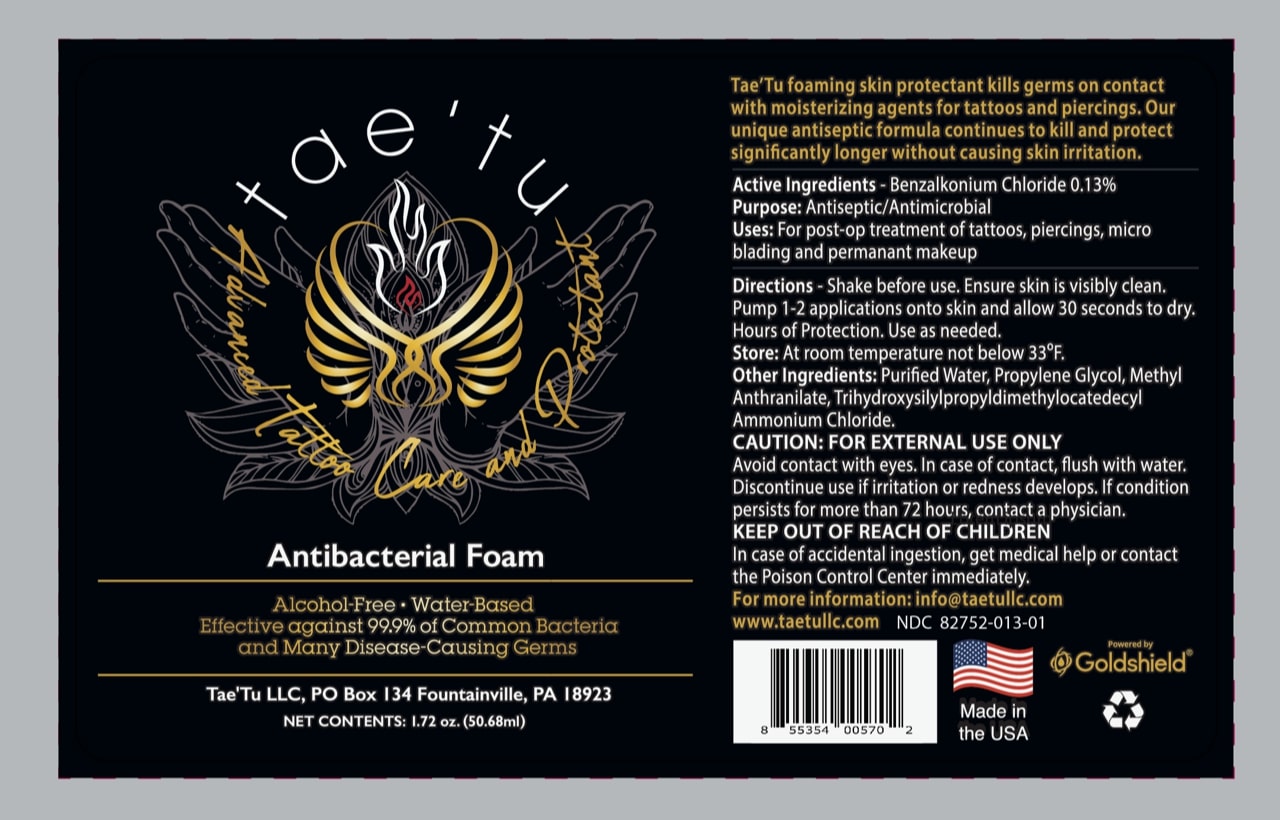 DRUG LABEL: TaeTu Aftercare
NDC: 82752-013 | Form: SOLUTION
Manufacturer: Taetu LLC
Category: otc | Type: HUMAN OTC DRUG LABEL
Date: 20231214

ACTIVE INGREDIENTS: BENZALKONIUM CHLORIDE 0.13 g/1 mL
INACTIVE INGREDIENTS: WATER 1 mL/1 mL

DESCRIPTION

Tae'Tu foaming skin protectant kills germs on contact with moisturizing agents for tattoos and piercings. Our unique antiseptic formula continues to kill and protect significantly longer without causing skin irritation.

Active Ingredients:

Benzalkonium Chloride 0.13%

Purpose:

Antiseptic/Antimicrobial

Uses:

For post-op treatment of tattoos, piercings, microblading, and permanent makeup.

Directions:

Shake before use. Ensure skin is visibly clean. Pump 1-2 applications onto skin and allow 30 seconds to dry. Hours of protection. Use as needed.

Store:

At room temperature not below 33°F.

Other Ingredients:

Purified water, propylene glycol, methyl anthranilate, trihydroxysilylpropyldimethylocatedecyl ammonium chloride.

CAUTION:

FOR EXTERNAL USE ONLY

Avoid contact with eyes. In case of contact, flush with water. Discontinue use if irritation or redness develops. If condition persists for more than 72 hours, contact a physician.

KEEP OUT OF REACH OF CHILDREN

In case of accidental ingestion, get medical help or contact the Poison Control Center immediately.

PACKAGE LABEL

Tae'Tu foaming skin protectant kills germs on contact with moisturizing agents for tattoos and piercings. Our unique antiseptic formula continues to kill and protect significantly longer without causing skin irritation.